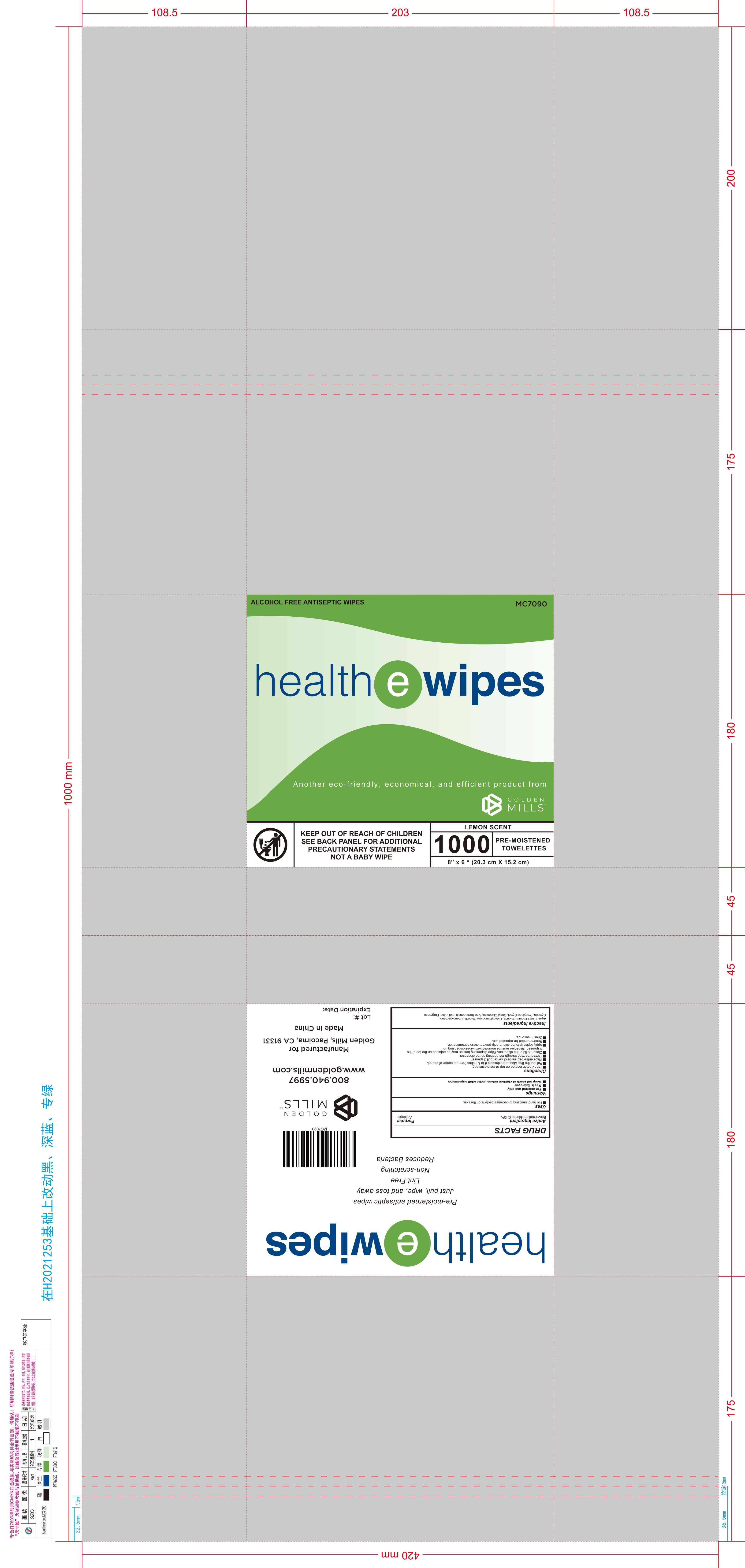 DRUG LABEL: Health E Wipes Lemon Scent 1000CT
NDC: 85989-003 | Form: PATCH
Manufacturer: Hangzhou Yida Technology Co., Ltd.
Category: otc | Type: HUMAN OTC DRUG LABEL
Date: 20251105

ACTIVE INGREDIENTS: BENZALKONIUM CHLORIDE 1.3 mg/1 g
INACTIVE INGREDIENTS: PHENOXYETHANOL; DIAZOLIDINYL UREA; BUTYLPARABEN; POLYOXYL 40 HYDROGENATED CASTOR OIL; WATER; METHYLPARABEN; PROPYLENE GLYCOL; PROPYLPARABEN; ISOBUTYLPARABEN; GLYCERIN; ETHYLPARABEN

ACTIVE INGREDIENT

Benzalkonium chloride 0.13% Purpose - Antiseptic

PURPOSE

For hand sanitizing to decrease bacteria on the skin.

Keep out of reach of children

unless under adult supervision

Warnings

For external use only
May irritate eyes

INDICATIONS AND USAGE

Tear V notch located on top of the plastic bag.
Pull out the first wipe approximately 6 to 8 inches from the center of the roll.
Place entire bag inside of center pull dispenser.
Thread the wipe through the opening on the dispenser.
Close the lid of the dispenser. Wipe dispensing tension may be adjusted on the top of the dispenser. Dispenser must be mounted with wipes dispensing up.
Apply topically to the skin to help prevent cross contamination.
Recommended for repeated use.
Dries in seconds.

DOSAGE AND ADMINISTRATION

Tear V notch located on top of the plastic bag.
Pull out the first wipe approximately 6 to 8 inches from the center of the roll.

INACTIVE INGREDIENT

Aloe barbadensis extract, diazolidinyl urea, fragrance, glycerin, lauryl betain, methylparaben/ethylparaben/propylparaben/butylparaben /isobutylparaben/phenoxyethanol, PEG-40 hydrogenated castor oil, propylene glycol, water.